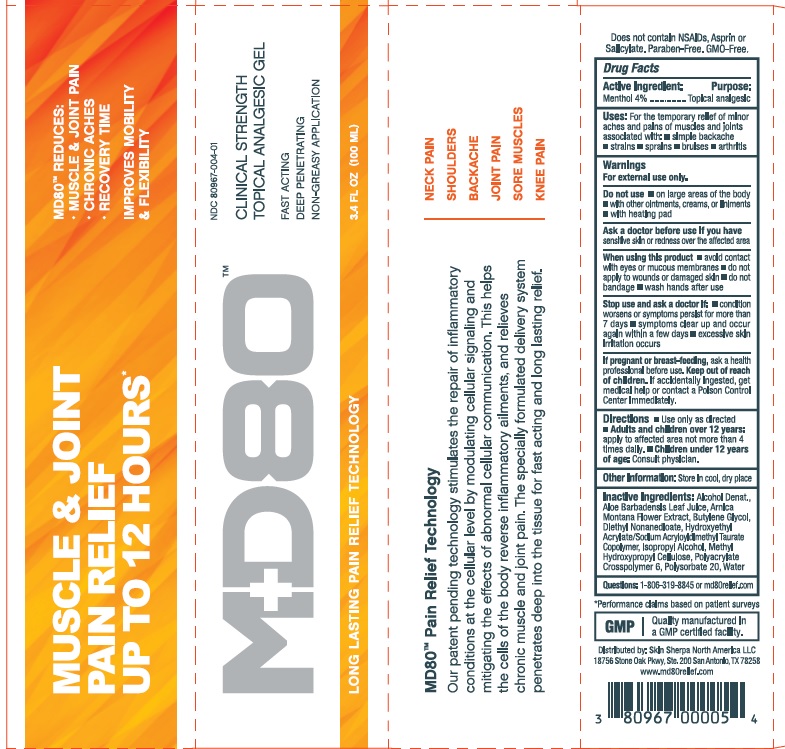 DRUG LABEL: MD80 CLINICAL STRENGTH TOPICAL ANALGESIC
NDC: 80967-004 | Form: GEL
Manufacturer: SKIN SHERPA NORTH AMERICA LLC
Category: otc | Type: HUMAN OTC DRUG LABEL
Date: 20220502

ACTIVE INGREDIENTS: MENTHOL 40 mg/1 mL
INACTIVE INGREDIENTS: AMMONIUM ACRYLOYLDIMETHYLTAURATE, DIMETHYLACRYLAMIDE, LAURYL METHACRYLATE AND LAURETH-4 METHACRYLATE COPOLYMER, TRIMETHYLOLPROPANE TRIACRYLATE CROSSLINKED (45000 MPA.S); ALCOHOL; POLYSORBATE 20; WATER; HYPROMELLOSE, UNSPECIFIED; DIETHYL AZELATE; ISOPROPYL ALCOHOL; ALOE VERA LEAF; BUTYLENE GLYCOL; ARNICA MONTANA FLOWER; HYDROXYETHYL ACRYLATE/SODIUM ACRYLOYLDIMETHYL TAURATE COPOLYMER (100000 MPA.S AT 1.5%)

MD80 CLINICAL STRENGTH TOPICAL ANALGESIC GEL

Active ingredient

Menthol 4%

Purpose

Topical analgesic

Uses

For the temporary relief of minor aches and pains of muscles and joints associated with:

- simple backache
- strains
- sprains
- bruises
- arthritis

Warnings

For external use only.

Do not use

- on large areas of the body
- with other ointments, creams, sprays or liniments
- with heating pad

Ask a doctor before use if you have

sensitive skin or redness over the affected area

When using this product

- avoid contact with eyes or mucous membranes
- do not apply to wounds or damaged skin
- do not bandage
- wash hands after use

Stop use and ask a doctor if

- condition worsens or symptoms persist for more than 7 days
- symptoms clear up and occur again within a few days
- excessive skin irritation occurs

If pregnant or breast-feeding

ask a health professional before use.

Keep out of reach of children.

If accidentally ingested, get medical help or contact a Poison Control Center immediately.

Directions

- Use only as directed
- Adults and children over 12 years: apply to affected area not more than 4 times daily.
- Children under 12 years of age: Consult physician.

Other information

Store in cool dry place

Inactive ingredients

Alcohol Denat., Aloe Barbadensis Leaf Juice, Arnica Montana Flower Extract, Butylene Glycol, Diethyl Nonanedioate, Hydroxyethyl Acrylate/Sodium Acryloyldimethyl Taurate Copolymer, Isopropyl Alcohol, Methyl Hydroxypropyl Cellulose, Polyacrylate Crosspolymer 6, Polysorbate 20, Water

Questions?

1-806-319-8845 or md80relief.com

Company Information

Distributed by Skin Sherpa North America, LLC, 18756 Stone Oak Pkwy, Ste. 200 San Antonio, TX 78258

www.md80relief.com